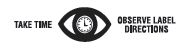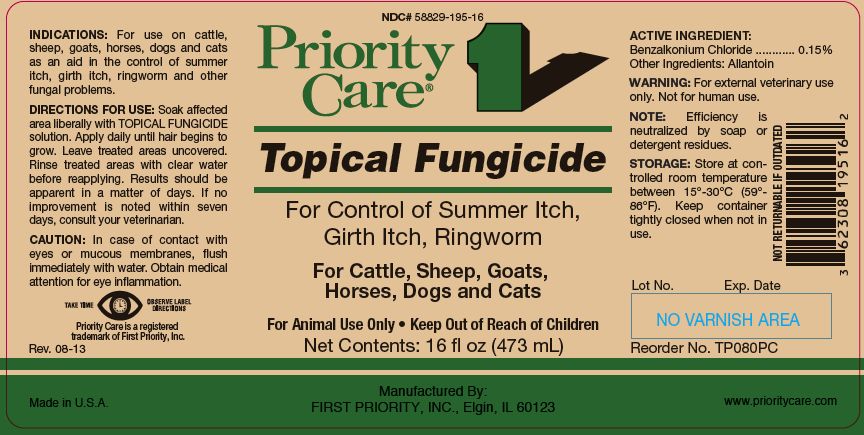 DRUG LABEL: Topical Fungicide
NDC: 58829-195 | Form: SOLUTION
Manufacturer: First Priority, Incorporated
Category: animal | Type: OTC ANIMAL DRUG LABEL
Date: 20260218

ACTIVE INGREDIENTS: BENZALKONIUM CHLORIDE 3.09 mg/1 mL

Topical Fungicide

PURPOSE

For Control of Summer Itch, Girth Itch, Ringworm

For Cattle, Sheep, Goats, Horses, Dogs and Cats

WARNINGS AND PRECAUTIONS

For Animal Use Only • Keep Out of Reach of Children

INDICATIONS:

For use on cattle, sheep, goats, horses, dogs and cats as an aid in the control of summer itch, girth itch, ringworm and other fungal problems.

DIRECTIONS FOR USE:

Soak affected area liberally with TOPICAL FUNGICIDE solution. Apply daily until hair begins to grow. Leave treated areas uncovered. Rinse treated areas with clear water before reapplying. Results should be apparent in a matter of days. If no improvement is noted within seven days, consult your veterinarian.

CAUTION:

In case of contact with eyes or mucous membranes, flush immediately with water. Obtain medical attention for eye inflammation.

ACTIVE INGREDIENT:

Benzalkonium chloride ......................0.15%

Other Ingredients:

Allantoin

WARNING:

For external veterinary use only. Not for human use.

NOTE:

Efficiency is neutralized by soap or detergent residues.

STORAGE:

Store at controlled room temperature between 15°-30°C (59°- 86°F). Keep container tightly closed when not in use.

Net Contents:

16 fl oz (473 mL) Reorder No. TP080PC

32 fl oz (960 mL) Reorder No. TP081PC

INFORMATION FOR OWNERS/CAREGIVERS

Priority Care is a registered trademark of First Priority, Inc.

Made in U.S.A.

Manufactured By: FIRST PRIORITY, INC., Elgin, IL 60123

www.prioritycare.com

NOT RETURNABLE IF OUTDATED